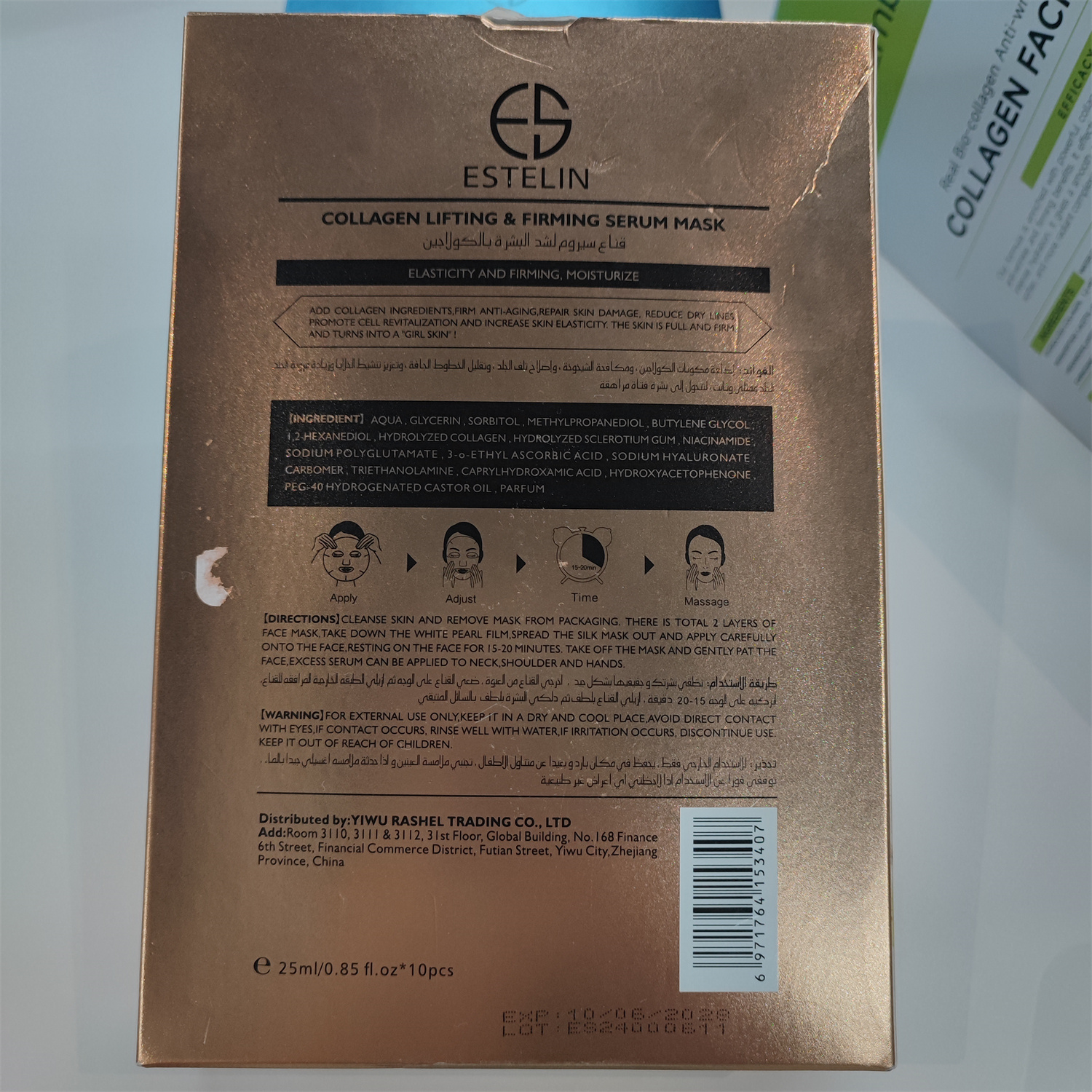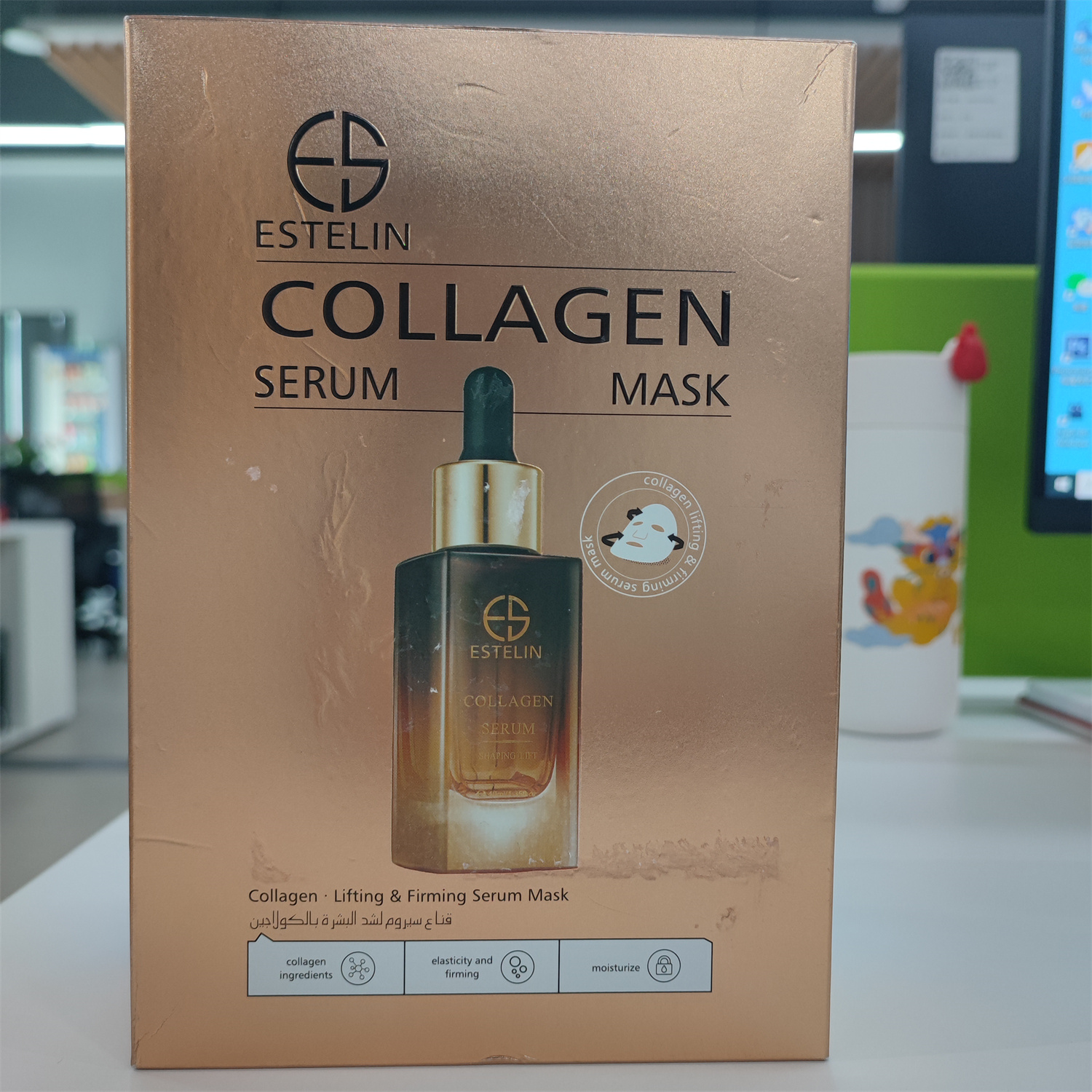 DRUG LABEL: ESTELIN COLLAGEN SERUM MASK
NDC: 84716-002 | Form: DRESSING
Manufacturer: Shenzhen Boyang E-commerce Co.
Category: otc | Type: HUMAN OTC DRUG LABEL
Date: 20241013

ACTIVE INGREDIENTS: SORBITOL 7.23 g/250 mL; GLYCERIN 7.23 g/250 mL; METHYLPROPANEDIOL 2.41 g/250 mL
INACTIVE INGREDIENTS: WATER 230.905 g/250 mL

ACTIVE INGREDIENTS

GLYCERIN 3%
SORBITOL 3%
METHYLPROPANEDIOL 1%

PURPOSE

ELASTICITY AND FIRMING, MOISTURIZE
ADD COLLAGEN INGREDIENTS,FIRM ANTI-AGING,REPAIR SKIN DAMAGE, REDUCE DRY LIVES,PROMOTE CELL REVITALIZATION AND INCREASE SKIN ELASTICITY。THE SKIN IS FULL AND FIRM，AND TURNS INTO A "GIRL SKIN" 。

Uses

CLEANSE SKIN AND REMOVE MASK FROM PACKAGING, THERE IS TOTAL 2 LAYERS OF FACE MASK,TAKE DOWN THE WHITE PEARL FILM,SPREAD THE SILK MASK OUT AND APPLY CAREFULLY ONTO THE FACE,RESTING ON THE FACE FOR I5-20 MINUTES. TAKE OFF THE MASK AND GENTLY PAT THE FACE,EXCESS SERUM CAN BE APPLIED TO NECK,SHOULDER AND HANDS.

Warnings

FOR EXTERNAL USE ONLY,

KEEP IT IN A DRY AND COOL PLACE,AVOID DIRECT CONTACT WITH EYES,IF CONTACT OCCURS, RINSE WELL WITH WATER IF IRRITATION OCCURS,

DISCONTINUE USEKEEP IT OUT OF REACH OF CHILDREN.

Stop use and ask a doctor if

lt is recommended to have a skin test (inside the wrist orbehind the ear) before use.If you feel uncomfortable,please stop using it.

Do not use

on damaged or broken skin.

Keep out of reach of children

Please place it out of the reach of infants；If swallowed, get medical help or contact a Poison Control Center right away.

When using this product

For external use only

keep out of eyes. Rinse with water to remove.

INACTIVE INGREDIENT SECTON

water

uses and storage method

USES:

CLEANSE SKIN AND REMOVE MASK FROM PACKAGING, THERE IS TOTAL 2 LAYERS OF FACE MASK,TAKE DOWN THE WHITE PEARL FILM,SPREAD THE SILK MASK OUT AND APPLY CAREFULLY ONTO THE FACE,RESTING ON THE FACE FOR I5-20 MINUTES. TAKE OFF THE MASK AND GENTLY PAT THE FACE,EXCESS SERUM CAN BE APPLIED TO NECK,SHOULDER AND HANDS.

FOR EXTERNAL USE ONLY,

KEEP IT IN A DRY AND COOL PLACE,AVOID DIRECT CONTACT WITH EYES,IF CONTACT OCCURS, RINSE WELL WITH WATER IF IRRITATION OCCURS,

DISCONTINUE USEKEEP IT OUT OF REACH OF CHILDREN.